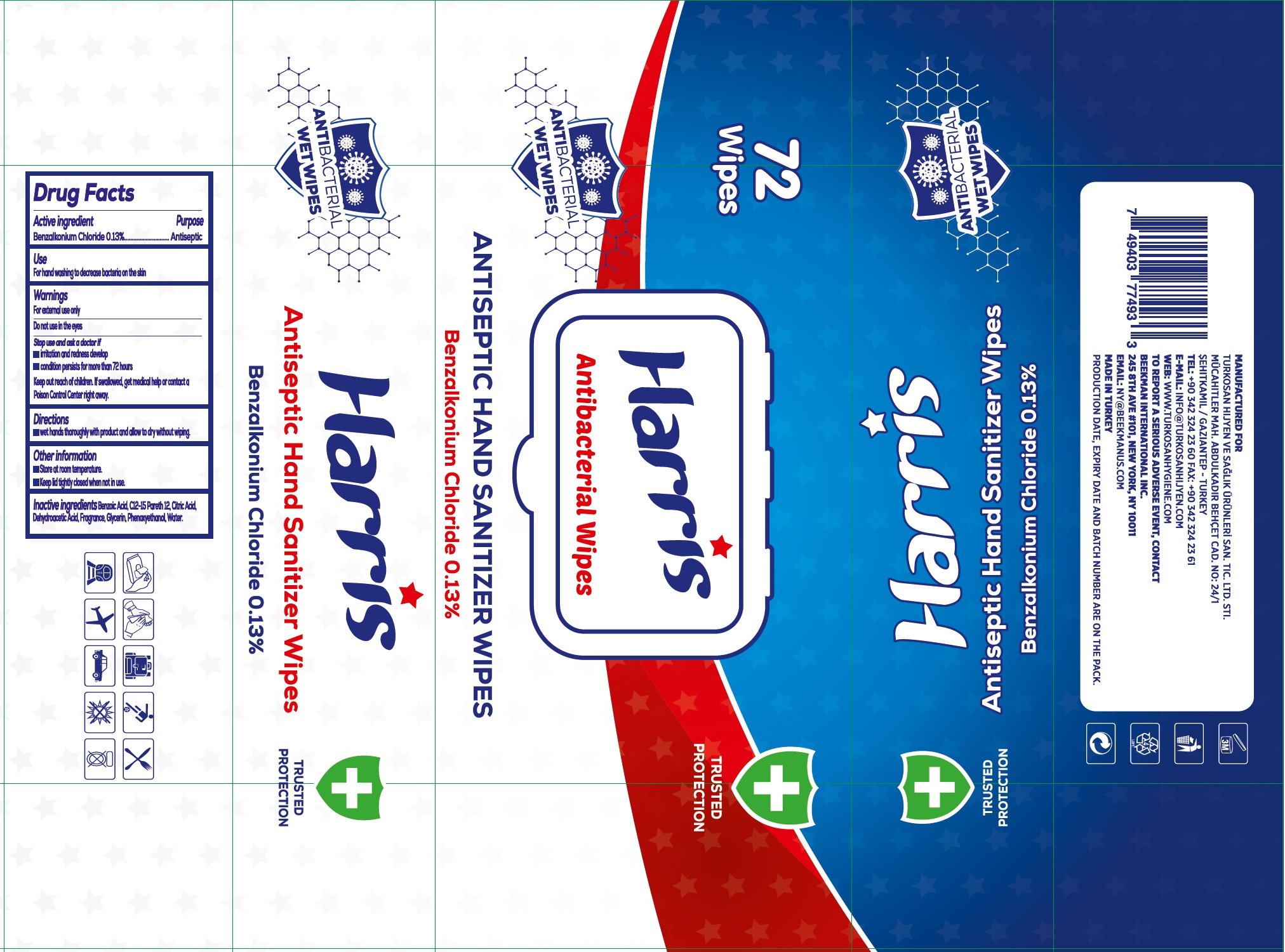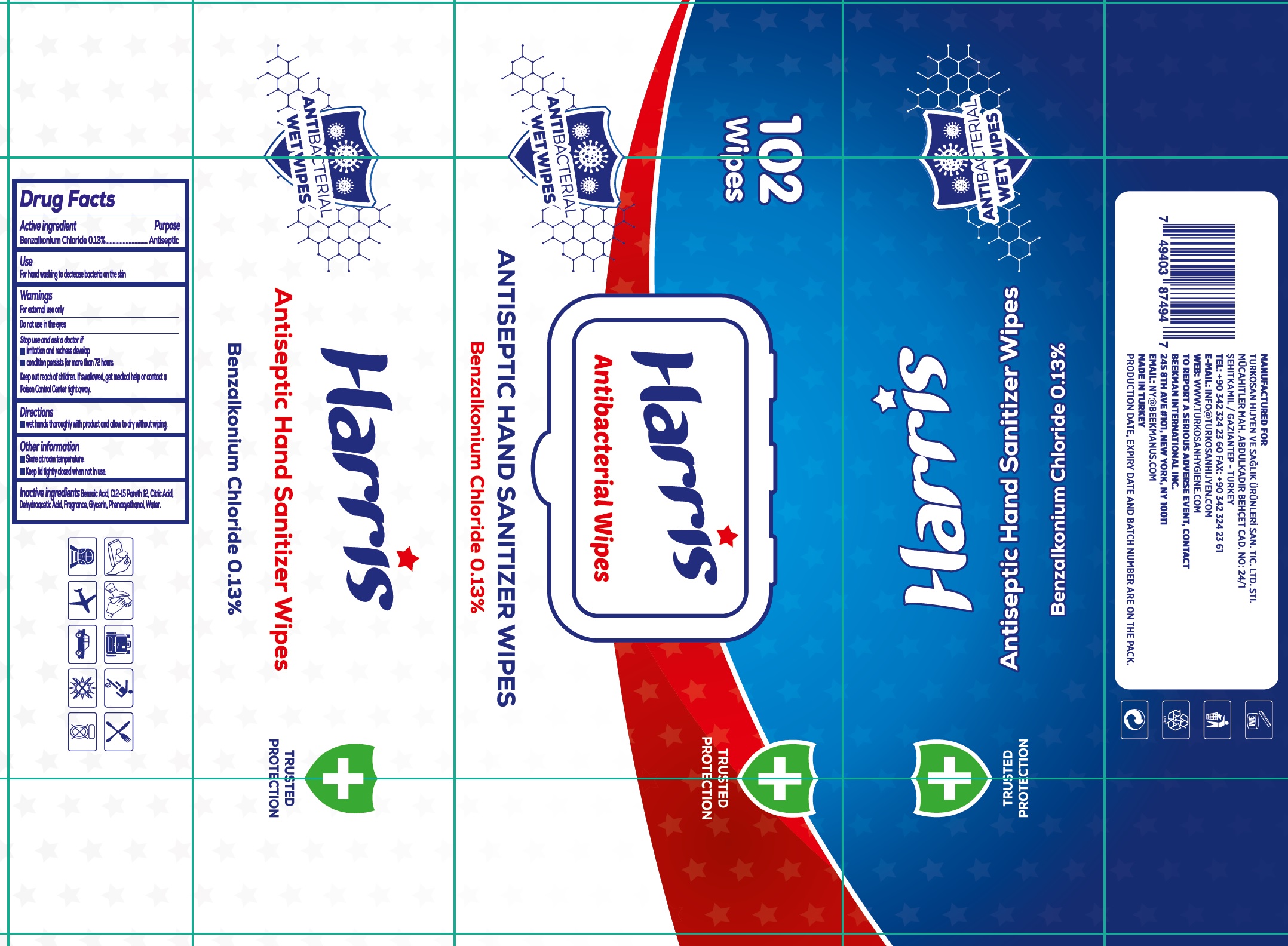 DRUG LABEL: Harris Antibacterial Wipes Antiseptic Hand Sanitizer Wipes
NDC: 80510-000 | Form: CLOTH
Manufacturer: TURKOSAN SAGLIK URUNLERI SANAYI VE TICARET ANONIM SIRKETI
Category: otc | Type: HUMAN OTC DRUG LABEL
Date: 20220322

ACTIVE INGREDIENTS: BENZALKONIUM CHLORIDE 1.3 mg/1 mL
INACTIVE INGREDIENTS: BENZOIC ACID; C12-15 PARETH-12; CITRIC ACID MONOHYDRATE; DEHYDROACETIC ACID; GLYCERIN; PHENOXYETHANOL; WATER

Harris Antibacterial Wipes Antiseptic Hand Sanitizer Wipes

Active ingredient

Benzalkonium Chloride 0.13%

Purpose

Antiseptic

Use

For hand washing to decrease bacteria on the skin

Warnings

For external use only

Do not use

in the eyes

Stop use and ask a doctor if

- irritation and redness develop
- condition persists for more than 72 hours

Keep out of reach of children.

If swallowed, get medical help or contact a Poison Control Center right away.

Directions

- wet hands thoroughly with product and allow to dry without wiping.

Other information

- Store at room temperature.
- Keep lid tightly closed when not in use.

Inactive ingredients

Benzoic Acid, C12-15 Pareth 12, Citric Acid, Dehydroacetic Acid, Fragrance, Glycerin, Phenoxyethanol, Water.